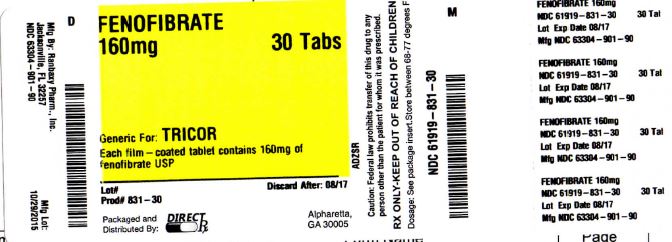 DRUG LABEL: FENOFIBRATE
NDC: 61919-831 | Form: TABLET, FILM COATED
Manufacturer: DirectRX
Category: prescription | Type: HUMAN PRESCRIPTION DRUG LABEL
Date: 20151029

ACTIVE INGREDIENTS: FENOFIBRATE 160 mg/1 1
INACTIVE INGREDIENTS: COLLOIDAL SILICON DIOXIDE; CROSPOVIDONE; LECITHIN, SOYBEAN; POLYVINYL ALCOHOL; CELLULOSE, MICROCRYSTALLINE; POVIDONE; STARCH, PREGELATINIZED CORN; SODIUM LAURETH SULFATE; SODIUM STEARYL FUMARATE; TALC; TITANIUM DIOXIDE; XANTHAN GUM

FENOFIBRATE

DESCRIPTION SECTION

Fenofibrate tablets, USP is a lipid regulating agent available as tablets for oral administration. Each tablet contains 54 mg or 160 mg of fenofibrate, USP. The chemical name for fenofibrate is 2-[4-(4-chlorobenzoyl) phenoxy]-2-methyl-propanoic acid, 1-methylethyl ester with the following molecular structure:

structure

The molecular formula is C20H21O4Cl and the molecular weight is 360.83; fenofibrate, USP is very soluble in methylene chloride, slightly soluble in alcohal and prectically insoluble in water. The melting point is 79 - 82° C. Fenofibrate, USP is a white or almost white crystalline powder.

Inactive Ingredients: Each tablet contains colloidal silicon dioxide, crospovidone, lecithin (soya), microcrystalline cellulose, polyvinyl alcohol, povidone, pregelatinized starch, sodium lauryl sulfate, sodium stearyl fumarate, talc, titanium dioxide and xanthan gum.

Meets USP Dissolution Test 2.

CLINICAL PHARMACOLOGY SECTION

- A variety of clinical studies have demonstrated that elevated levels of total cholesterol (total-C), low density lipoprotein cholesterol (LDL-C), and apolipoprotein B (apo B), an LDL membrane complex, are associated with human atherosclerosis. Similarly, decreased levels of high density lipoprotein cholesterol (HDL-C) and its transport complex, apolipoprotein A (apo AI and apo AII) are associated with the development of atherosclerosis. Epidemiologic investigations have established that cardiovascular morbidity and mortality vary directly with the level of total-C, LDL-C, and triglycerides, and inversely with the level of HDL-C. The independent effect of raising HDL-C or lowering triglycerides (TG) on the risk of cardiovascular morbidity and mortality has not been determined.
  Fenofibric acid, the active metabolite of fenofibrate, produces reductions in total cholesterol, LDL cholesterol, apolipoprotein B, total triglycerides and triglyceride rich lipoprotein (VLDL) in treated patients. In addition, treatment with fenofibrate results in increases in high density lipoprotein (HDL) and apoproteins apoAI and apoAII.
  The effects of fenofibric acid seen in clinical practice have been explained in vivo in transgenic mice and in vitro in human hepatocyte cultures by the activation of peroxisome proliferator activated receptor α (PPARα). Through this mechanism, fenofibrate increases lipolysis and elimination of triglyceride-rich particles from plasma by activating lipoprotein lipase and reducing production of apoprotein C-III (an inhibitor of lipoprotein lipase activity).
  The resulting fall in triglycerides produces an alteration in the size and composition of LDL from small, dense particles (which are thought to be atherogenic due to their susceptibility to oxidation), to large buoyant particles. These larger particles have a greater affinity for cholesterol receptors and are catabolized rapidly. Activation of PPARα also induces an increase in the synthesis of apoproteins A-I, A-II and HDL-cholesterol.
  Fenofibrate also reduces serum uric acid levels in hyperuricemic and normal individuals by increasing the urinary excretion of uric acid.
  Pharmacokinetics/Metabolism
  Plasma concentrations of fenofibric acid after administration of 54 mg and 160 mg tablets are equivalent under fed conditions to 67 and 200 mg capsules, respectively.
  Absorption
  The absolute bioavailability of fenofibrate cannot be determined as the compound is virtually insoluble in aqueous media suitable for injection. However, fenofibrate is well absorbed from the gastrointestinal tract. Following oral administration in healthy volunteers, approximately 60% of a single dose of radiolabelled fenofibrate appeared in urine, primarily as fenofibric acid and its glucuronate conjugate, and 25% was excreted in the feces. Peak plasma levels of fenofibric acid occur within 6 to 8 hours after administration.
  The absorption of fenofibrate is increased when administered with food. With fenofibrate tablets, the extent of absorption is increased by approximately 35% under fed as compared to fasting conditions.
  Distribution
  In healthy volunteers, steady-state plasma levels of fenofibric acid were shown to be achieved within 5 days of dosing and did not demonstrate accumulation across time following multiple dose administration. Serum protein binding was approximately 99% in normal and hyperlipidemic subjects.
  Metabolism
  Following oral administration, fenofibrate is rapidly hydrolyzed by esterases to the active metabolite, fenofibric acid; no unchanged fenofibrate is detected in plasma.
  Fenofibric acid is primarily conjugated with glucuronic acid and then excreted in urine. A small amount of fenofibric acid is reduced at the carbonyl moiety to a benzhydrol metabolite which is, in turn, conjugated with glucuronic acid and excreted in urine.
  In vivo metabolism data indicate that neither fenofibrate nor fenofibric acid undergo oxidative metabolism (e.g., cytochrome P450) to a significant extent.
  Excretion
  After absorption, fenofibrate is mainly excreted in the urine in the form of metabolites, primarily fenofibric acid and fenofibric acid glucuronide. After administration of radiolabelled fenofibrate, approximately 60% of the dose appeared in the urine and 25% was excreted in the feces.
  Fenofibric acid is eliminated with a half-life of 20 hours, allowing once daily administration in a clinical setting.
  Special populations
  Geriatrics
  In elderly volunteers 77 to 87 years of age, the oral clearance of fenofibric acid following a single oral dose of fenofibrate was 1.2 L/h, which compares to 1.1 L/h in young adults. This indicates that a similar dosage regimen can be used in the elderly, without increasing accumulation of the drug or metabolites.
  Pediatrics
  Fenofibrate tablets have not been investigated in adequate and well-controlled trials in pediatric patients.
  Gender
  No pharmacokinetic difference between males and females has been observed for fenofibrate.
  Race
  The influence of race on the pharmacokinetics of fenofibrate has not been studied, however fenofibrate is not metabolized by enzymes known for exhibiting inter-ethnic variability. Therefore, inter-ethnic pharmacokinetic differences are very unlikely.
  Renal insufficiency
  In a study in patients with severe renal impairment (creatinine clearance < 50 mL/min), the rate of clearance of fenofibric acid was greatly reduced, and the compound accumulated during chronic dosage. However, in patients having moderate renal impairment (creatinine clearance of 50 to 90 mL/min), the oral clearance and the oral volume of distribution of fenofibric acid are increased compared to healthy adults (2.1 L/h and 95 L versus 1.1 L/h and 30 L, respectively). Therefore, the dosage of fenofibrate tablets should be minimized in patients who have severe renal impairment, while no modification of dosage is required in patients having moderate renal impairment.
  Hepatic insufficiency
  No pharmacokinetic studies have been conducted in patients having hepatic insufficiency.
  Drug-drug interactions
  In vitro studies using human liver microsomes indicate that fenofibrate and fenofibric acid are not inhibitors of cytochrome (CYP) P450 isoforms CYP3A4, CYP2D6, CYP2E1, or CYP1A2. They are weak inhibitors of CYP2C19 and CYP2A6, and mild-to-moderate inhibitors of CYP2C9 at therapeutic concentrations.
  Potentiation of coumarin-type anticoagulants has been observed with prolongation of the prothrombin time/INR.
  Bile acid sequestrants have been shown to bind other drugs given concurrently. Therefore, fenofibrate should be taken at least 1 hour before or 4 to 6 hours after a bile acid binding resin to avoid impeding its absorption. (See WARNINGS and PRECAUTIONS).
  Clinical Trials
  Hypercholesterolemia (Heterozygous Familial and Nonfamilial) and Mixed Dyslipidemia (Fredrickson Types IIa and IIb)
  The effects of fenofibrate at a dose equivalent to 160 mg of fenofibrate tablets per day were assessed from four randomized, placebo-controlled, double-blind, parallel-group studies including patients with the following mean baseline lipid values: total-C 306.9 mg/dL; LDL-C 213.8 mg/dL; HDL-C 52.3 mg/dL; and triglycerides 191 mg/dL. Fenofibrate tablet therapy lowered LDL-C, Total-C, and the LDL-C/HDL-C ratio. Fenofibrate tablet therapy also lowered triglycerides and raised HDL-C (see Table 1).
  Table 1 Mean Percent Change in Lipid Parameters at End of Treatment†
  Treatment Group | Total-C | LDL-C | HDL-C | TG
  Pooled Cohort
  Mean baseline lipid values (n = 646) | 306.9 mg/dL | 213.8 mg/dL | 52.3 mg/dL | 191 mg/dL
  All FEN (n = 361) | -18.7%* | -20.6%* | +11%* | -28.9%*
  Placebo (n = 285) | -0.4% | -2.2% | +0.7% | +7.7%
  Baseline LDL-C > 160 mg/dL and
  TG < 150 mg/dL (Type IIa)
  Mean baseline lipid values (n = 334) | 307.7 mg/dL | 227.7 mg/dL | 58.1 mg/dL | 101.7 mg/dL
  All FEN (n = 193) | -22.4%* | -31.4%* | +9.8%* | -23.5%*
  Placebo (n = 141) | +0.2% | -2.2% | +2.6% | +11.7%
  Baseline LDL-C > 160 mg/dL and TG ≥ 150 mg/dL (Type IIb)
  Mean baseline lipid values (n = 242) | 312.8 mg/dL | 219.8 mg/dL | 46.7 mg/dL | 231.9 mg/dL
  All FEN (n = 126) | -16.8%* | -20.1%* | +14.6%* | -35.9%*
  Placebo (n = 116) | -3% | -6.6% | +2.3% | +0.9%
  †Duration of study treatment was 3 to 6 months.
  *p = < 0.05 vs. Placebo
  In a subset of the subjects, measurements of apo B were conducted. Fenofibrate tablet treatment significantly reduced apo B from baseline to endpoint as compared with placebo (-25.1% vs. 2.4%, p < 0.0001, n = 213 and 143 respectively).
  Hypertriglyceridemia (Fredrickson Type IV and V)
  The effects of fenofibrate on serum triglycerides were studied in two randomized, double-blind, placebo-controlled clinical trials1 of 147 hypertriglyceridemic patients (Fredrickson Types IV and V). Patients were treated for eight weeks under protocols that differed only in that one entered patients with baseline triglyceride (TG) levels of 500 to 1500 mg/dL, and the other TG levels of 350 to 500 mg/dL. In patients with hypertriglyceridemia and normal cholesterolemia with or without hyperchylomicronemia (Type IV/V hyperlipidemia), treatment with fenofibrate at dosages equivalent to 160 mg of fenofibrate tablets per day decreased primarily very low density lipoprotein (VLDL) triglycerides and VLDL cholesterol. Treatment of patients with Type IV hyperlipoproteinemia and elevated triglycerides often results in an increase of low density lipoprotein (LDL) cholesterol (see Table 2).
  Table 2 Effects of Fenofibrate Tablets in Patients With Fredrickson Type IV/V Hyperlipidemia
  Study 1 |  | Placebo |  |  | Fenofibrate Tablets
  Baseline TG level |  | Baseline | Endpoint | % Change |  | Baseline | Endpoint | % Change
  350 to 499 mg/dL | N | (Mean) | (Mean) | (Mean) | N | (Mean) | (Mean) | (Mean)
  Triglycerides | 28 | 449 | 450 | -0.5 | 27 | 432 | 223 | -46.2*
  VLDL Triglycerides | 19 | 367 | 350 | 2.7 | 19 | 350 | 178 | -44.1*
  Total Cholesterol | 28 | 255 | 261 | 2.8 | 27 | 252 | 227 | -9.1*
  HDL Cholesterol | 28 | 35 | 36 | 4 | 27 | 34 | 40 | 19.6*
  LDL Cholesterol | 28 | 120 | 129 | 12 | 27 | 128 | 137 | 14.5
  VLDL Cholesterol | 27 | 99 | 99 | 5.8 | 27 | 92 | 46 | -44.7*
  Study 2 |  | Placebo |  |  | Fenofibrate Tablets
  Baseline TG level |  | Baseline | Endpoint | % Change |  | Baseline | Endpoint | % Change
  500 to 1500 mg/dL | N | (Mean) | (Mean) | (Mean) | N | (Mean) | (Mean) | (Mean)
  Triglycerides | 44 | 710 | 750 | 7.2 | 48 | 726 | 308 | -54.5*
  VLDL Triglycerides | 29 | 537 | 571 | 18.7 | 33 | 543 | 205 | -50.6*
  Total Cholesterol | 44 | 272 | 271 | 0.4 | 48 | 261 | 223 | -13.8*
  HDL Cholesterol | 44 | 27 | 28 | 5 | 48 | 30 | 36 | 22.9*
  LDL Cholesterol | 42 | 100 | 90 | -4.2 | 45 | 103 | 131 | 45*
  VLDL Cholesterol | 42 | 137 | 142 | 11 | 45 | 126 | 54 | -49.4*
  *= p < 0.05 vs. Placebo
  The effect of fenofibrate tablets on cardiovascular morbidity and mortality has not been determined.

INDICATIONS & USAGE SECTION

- Treatment of Hypercholesterolemia
  Fenofibrate tablets, USP are indicated as adjunctive therapy to diet to reduce elevated LDL-C, Total-C, Triglycerides and Apo B, and to increase HDL-C in adult patients with primary hypercholesterolemia or mixed dyslipidemia (Fredrickson Types IIa and IIb). Lipid-altering agents should be used in addition to a diet restricted in saturated fat and cholesterol when response to diet and non-pharmacological interventions alone has been inadequate (See National Cholesterol Education Program [NCEP] Treatment Guidelines, below).
  Treatment of Hypertriglyceridemia
  Fenofibrate tablets, USP are also indicated as adjunctive therapy to diet for treatment of adult patients with hypertriglyceridemia (Fredrickson Types IV and V hyperlipidemia). Improving glycemic control in diabetic patients showing fasting chylomicronemia will usually reduce fasting triglycerides and eliminate chylomicronemia thereby obviating the need for pharmacologic intervention.
  Markedly elevated levels of serum triglycerides (e.g. > 2,000 mg/dL) may increase the risk of developing pancreatitis. The effect of fenofibrate tablet, USP therapy on reducing this risk has not been adequately studied.
  Drug therapy is not indicated for patients with Type I hyperlipoproteinemia, who have elevations of chylomicrons and plasma triglycerides, but who have normal levels of very low density lipoprotein (VLDL). Inspection of plasma refrigerated for 14 hours is helpful in distinguishing Types I, IV and V hyperlipoproteinemia2.
  The initial treatment for dyslipidemia is dietary therapy specific for the type of lipoprotein abnormality. Excess body weight and excess alcoholic intake may be important factors in hypertriglyceridemia and should be addressed prior to any drug therapy. Physical exercise can be an important ancillary measure. Diseases contributory to hyperlipidemia, such as hypothyroidism or diabetes mellitus should be looked for and adequately treated. Estrogen therapy, thiazide diuretics and beta-blockers, are sometimes associated with massive rises in plasma triglycerides, especially in subjects with familial hypertriglyceridemia. In such cases, discontinuation of the specific etiologic agent may obviate the need for specific drug therapy of hypertriglyceridemia.
  The use of drugs should be considered only when reasonable attempts have been made to obtain satisfactory results with non-drug methods. If the decision is made to use drugs, the patient should be instructed that this does not reduce the importance of adhering to diet. (See WARNINGS and PRECAUTIONS).
  Fredrickson Classification of Hyperlipoproteinemias
   | Lipid Elevation
  Type | Lipoprotein Elevated | Major | Minor
  I (rare) | chylomicrons | TG | ↑↔C
  IIa | LDL | C | -
  IIb | LDL, VLDL | C | TG
  III (rare) | IDL | C, TG | -
  IV | VLDL | TG | ↑↔C
  V (rare) | chylomicrons, VLDL | TG | ↑↔
  C = cholesterol
  TG = triglycerides
  LDL = low density lipoprotein
  VLDL = very low density lipoprotein
  IDL = intermediate density lipoprotein
  NCEP Treatment Guidelines: LDL-C Goals and Cutpoints for Therapeutic Lifestyle Changes and Drug Therapy in Different Risk Categories
  Risk Category | LDL Goal (mg/dL) | LDL Level at Which to Initiate Therapeutic Lifestyle Changes (mg/dL) | LDL Level at Which to Consider Drug Therapy (mg/dL)
  CHD† or CHD risk equivalents (10-years risk > 20%) | < 100 | ≥ 100 | ≥ 130 (100 to 129: drug optional)††
  2+ Risk Factors (10-year risk ≤ 20%) | < 130 | ≥ 130 | 10-year risk 10% to 20%: ≥ 130 10-year risk < 10%: ≥ 160
  0 to 1 Risk Factor††† | < 160 | ≥ 160 | ≥ 190 (160 to 189: LDL- lowering drug optional)
  †CHD = coronary heart disease
  ††Some authorities recommend use of LDL-lowering drugs in this category if an LDL-C level of < 100 mg/dL cannot be achieved by therapeutic lifestyle changes. Others prefer use of drugs that primarily modify triglycerides and HDL-C, e.g., nicotinic acid or fibrate. Clinical judgment also may call for deferring drug therapy in this subcategory.
  †††Almost all people with 0 to 1 risk factor have 10-year risk < 10%; thus, 10-year risk assessment in people with 0 to 1 risk factor is not necessary.
  After the LDL-C goal has been achieved, if the TG is still ≥ 200 mg/dL, non HDL-C (total-C minus HDL-C) becomes a secondary target of therapy. Non-HDL-C goals are set 30 mg/dL higher than LDL-C goals for each risk category.

CONTRAINDICATIONS SECTION

Fenofibrate tablets are contraindicated in patients who exhibit hypersensitivity to fenofibrate.

Fenofibrate tablets are contraindicated in patients with hepatic or severe renal dysfunction, including primary biliary cirrhosis, and patients with unexplained persistent liver function abnormality.

Fenofibrate tablets are contraindicated in patients with preexisting gallbladder disease (See WARNINGS).

WARNINGS SECTION

- Liver Function: Fenofibrate at doses equivalent to 107 mg to 160 mg fenofibrate tablets per day has been associated with increases in serum transaminases [AST (SGOT) or ALT (SGPT)]. In a pooled analysis of 10 placebo-controlled trials, increases to > 3 times the upper limit of normal occurred in 5.3% of patients taking fenofibrate versus 1.1% of patients treated with placebo.
  When transaminase determinations were followed either after discontinuation of treatment or during continued treatment, a return to normal limits was usually observed. The incidence of increases in transaminases related to fenofibrate therapy appears to be dose related. In an 8-week dose-ranging study, the incidence of ALT or AST elevations to at least three times the upper limit of normal was 13% in patients receiving dosages equivalent to 107 mg to 160 mg of fenofibrate tablets per day and was 0% in those receiving dosages equivalent to 54 mg or less of fenofibrate tablets per day, or placebo. Hepatocellular, chronic active and cholestatic hepatitis associated with fenofibrate therapy have been reported after exposures of weeks to several years. In extremely rare cases, cirrhosis has been reported in association with chronic active hepatitis.
  Regular periodic monitoring of liver function, including serum ALT (SGPT) should be performed for the duration of therapy with fenofibrate tablets, and therapy discontinued if enzyme levels persist above three times the normal limit.
  Cholelithiasis: Fenofibrate, like clofibrate and gemfibrozil, may increase cholesterol excretion into the bile, leading to cholelithiasis. If cholelithiasis is suspected, gallbladder studies are indicated. Fenofibrate tablet therapy should be discontinued if gallstones are found.
  Concomitant Oral Anticoagulants: Caution should be exercised when anticoagulants are given in conjunction with fenofibrate tablets because of the potentiation of coumarin-type anticoagulants in prolonging the prothrombin time/INR. The dosage of the anticoagulant should be reduced to maintain the prothrombin time/INR at the desired level to prevent bleeding complications. Frequent prothrombin time/INR determinations are advisable until it has been definitely determined that the prothrombin time/INR has stabilized.
  Concomitant HMG-CoA Reductase Inhibitors: The combined use of fenofibrate tablets and HMG-CoA reductase inhibitors should be avoided unless the benefit of further alterations in lipid levels is likely to outweigh the increased risk of this drug combination.
  In a single-dose drug interaction study in 23 healthy adults the concomitant administration of fenofibrate tablets and pravastatin resulted in no clinically important difference in the pharmacokinetics of fenofibric acid, pravastatin or its active metabolite 3a-hydroxy iso-pravastatin when compared to either drug given alone.
  The combined use of fibric acid derivatives and HMG-CoA reductase inhibitors has been associated, in the absence of a marked pharmacokinetic interaction, in numerous case reports, with rhabdomyolysis, markedly elevated creatine kinase (CK) levels and myoglobinuria, leading in a high proportion of cases to acute renal failure.
  The use of fibrates alone, including fenofibrate tablets, may occasionally be associated with myositis, myopathy, or rhabdomyolysis. Patients receiving fenofibrate tablets and complaining of muscle pain, tenderness, or weakness should have prompt medical evaluation for myopathy, including serum creatine kinase level determination. If myopathy/myositis is suspected or diagnosed, fenofibrate tablets therapy should be stopped.
  Mortality: The effect of fenofibrate tablets on coronary heart disease morbidity and mortality and noncardiovascular mortality has not been established.
  Other Considerations: In the Coronary Drug Project, a large study of post myocardial infarction of patients treated for 5 years with clofibrate, there was no difference in mortality seen between the clofibrate group and the placebo group. There was however, a difference in the rate of cholelithiasis and cholecystitis requiring surgery between the two groups (3% vs. 1.8%).
  Because of chemical, pharmacological, and clinical similarities between fenofibrate tablets, Atromid-S (clofibrate), and Lopid (gemfibrozil), the adverse findings in 4 large randomized, placebo-controlled clinical studies with these other fibrate drugs may also apply to fenofibrate tablets.
  In a study conducted by the World Health Organization (WHO), 5000 subjects without known coronary artery disease were treated with placebo or clofibrate for 5 years and followed for an additional one year. There was a statistically significant, higher age-adjusted all-cause mortality in the clofibrate group compared with the placebo group (5.70% vs. 3.96%, p = < 0.01). Excess mortality was due to a 33% increase in non-cardiovascular causes, including malignancy, post-cholecystectomy complications, and pancreatitis. This appeared to confirm the higher risk of gallbladder disease seen in clofibrate-treated patients studied in the Coronary Drug Project.
  The Helsinki Heart Study was a large (n = 4081) study of middle-aged men without a history of coronary artery disease. Subjects received either placebo or gemfibrozil for 5 years, with a 3.5 year open extension afterward. Total mortality was numerically higher in the gemfibrozil randomization group but did not achieve statistical significance (p = 0.19, 95% confidence interval for relative risk G:P = 0.91 to 1.64). Although cancer deaths trended higher in the gemfibrozil group (p = 0.11), cancers (excluding basal cell carcinoma) were diagnosed with equal frequency in both study groups. Due to the limited size of the study, the relative risk of death from any cause was not shown to be different than that seen in the 9 year follow-up data from World Health Organization study (RR = 1.29). Similarly, the numerical excess of gallbladder surgeries in the gemfibrozil group did not differ statistically from that observed in the WHO study.
  A secondary prevention component of the Helsinki Heart Study enrolled middle-aged men excluded from the primary prevention study because of known or suspected coronary heart disease. Subjects received gemfibrozil or placebo for 5 years. Although cardiac deaths trended higher in the gemfibrozil group, this was not statistically significant (hazard ratio 2.2, 95% confidence interval: 0.94 to 5.05). The rate of gallbladder surgery was not statistically significant between study groups, but did trend higher in the gemfibrozil group, (1.9% vs 0.3%, p = 0.07).
  There was a statistically significant difference in the number of appendectomies in the gemfibrozil group (6/311 vs. 0/317, p = 0.029).

PRECAUTIONS SECTION

- Initial Therapy: Laboratory studies should be done to ascertain that the lipid levels are consistently abnormal before instituting fenofibrate tablet therapy. Every attempt should be made to control serum lipids with appropriate diet, exercise, weight loss in obese patients, and control of any medical problems such as diabetes mellitus, and hypothyroidism that are contributing to the lipid abnormalities. Medications known to exacerbate hypertriglyceridemia (beta-blockers, thiazides, estrogens) should be discontinued or changed if possible prior to consideration of triglyceride-lowering drug therapy.
  Continued therapy: Periodic determination of serum lipids should be obtained during initial therapy in order to establish the lowest effective dose of fenofibrate tablets. Therapy should be withdrawn in patients who do not have an adequate response after two months of treatment with the maximum recommended dose of 160 mg per day.
  Pancreatitis: Pancreatitis has been reported in patients taking fenofibrate, gemfibrozil, and clofibrate. This occurrence may represent a failure of efficacy in patients with severe hypertriglyceridemia, a direct drug effect, or a secondary phenomenon mediated through biliary tract stone or sludge formation with obstruction of the common bile duct.
  Hypersensitivity Reactions: Acute hypersensitivity reactions including severe skin rashes requiring patient hospitalization and treatment with steroids have occurred very rarely during treatment with fenofibrate, including rare spontaneous reports of Stevens-Johnson syndrome, and toxic epidermal necrolysis. Urticaria was seen in 1.1 vs 0%, and rash in 1.4 vs 0.8% of fenofibrate and placebo patients respectively in controlled trials.
  Hematologic Changes: Mild to moderate hemoglobin, hematocrit, and white blood cell decreases have been observed in patients following initiation of fenofibrate therapy. However, these levels stabilize during long-term administration. Extremely rare spontaneous reports of thrombocytopenia and agranulocytosis have been received during post-marketing surveillance outside of the U.S. Periodic blood counts are recommended during the first 12 months of fenofibrate tablet administration.
  Skeletal muscle: The use of fibrates alone, including fenofibrate tablets may occasionally be associated with myopathy. Treatment with drugs of the fibrate class has been associated on rare occasions with rhabdomyolysis, usually in patients with impaired renal function. Myopathy should be considered in any patient with diffuse myalgias, muscle tenderness or weakness, and/or marked elevations of creatine phosphokinase levels.
  Patients should be advised to report promptly unexplained muscle pain, tenderness or weakness, particularly if accompanied by malaise or fever. CPK levels should be assessed in patients reporting these symptoms, and fenofibrate therapy should be discontinued if markedly elevated CPK levels occur or myopathy is diagnosed.
  Drug Interactions
  Oral Anticoagulants: CAUTION SHOULD BE EXERCISED WHEN COUMARIN ANTICOAGULANTS ARE GIVEN IN CONJUNCTION WITH FENOFIBRATE TABLETS. THE DOSAGE OF THE ANTICOAGULANTS SHOULD BE REDUCED TO MAINTAIN THE PROTHROMBIN TIME/INR AT THE DESIRED LEVEL TO PREVENT BLEEDING COMPLICATIONS. FREQUENT PROTHROMBIN TIME/INR DETERMINATIONS ARE ADVISABLE UNTIL IT HAS BEEN DEFINITELY DETERMINED THAT THE PROTHROMBIN TIME/INR HAS STABILIZED.
  HMG-CoA reductase inhibitors: The combined use of fenofibrate tablets and HMG-CoA reductase inhibitors should be avoided unless the benefit of further alterations in lipid levels is likely to outweigh the increased risk of this drug combination (See WARNINGS).
  Resins: Since bile acid sequestrants may bind other drugs given concurrently, patients should take fenofibrate tablets at least 1 hour before or 4 to 6 hours after a bile acid binding resin to avoid impeding its absorption.
  Cyclosporine: Because cyclosporine can produce nephrotoxicity with decreases in creatinine clearance and rises in serum creatinine, and because renal excretion is the primary elimination route of fibrate drugs including fenofibrate tablets, there is a risk that an interaction will lead to deterioration. The benefits and risks of using fenofibrate tablets with immunosuppressants and other potentially nephrotoxic agents should be carefully considered, and the lowest effective dose employed.
  Carcinogenesis, Mutagenesis, Impairment of Fertility: In a 24-month study in rats (10, 45, and 200 mg/kg; 0.3, 1, and 6 times the maximum recommended human dose on the basis of mg/meter2 of surface area), the incidence of liver carcinoma was significantly increased at 6 times the maximum recommended human dose in males and females. A statistically significant increase in pancreatic carcinomas occurred in males at 1 and 6 times the maximum recommended human dose; there were also increases in pancreatic adenomas and benign testicular interstitial cell tumors at 6 times the maximum recommended human dose in males. In a second 24-month study in a different strain of rats (doses of 10 and 60 mg/kg; 0.3 and 2 times the maximum recommended human dose based on mg/meter2 surface area), there were significant increases in the incidence of pancreatic acinar adenomas in both sexes and increases in interstitial cell tumors of the testes at 2 times the maximum recommended human dose.
  A comparative carcinogenicity study was done in rats comparing three drugs: fenofibrate (10 and 70 mg/kg; 0.3 and 1.6 times the maximum recommended human dose), clofibrate (400 mg/kg; 1.6 times the human dose), and gemfibrozil (250 mg/kg; 1.7 times the human dose) (multiples based on mg/meter2 surface area). Pancreatic acinar adenomas were increased in males and females on fenofibrate; hepatocellular carcinoma and pancreatic acinar adenomas were increased in males and hepatic neoplastic nodules in females treated with clofibrate; hepatic neoplastic nodules were increased in males and females treated with gemfibrozil while testicular interstitial cell tumors were increased in males on all three drugs.
  In a 21-month study in mice at doses of 10, 45, and 200 mg/kg (approximately 0.2, 0.7 and 3 times the maximum recommended human dose on the basis of mg/meter2 surface area), there were statistically significant increases in liver carcinoma at 3 times the maximum recommended human dose in both males and females. In a second 18-month study at the same doses, there was a significant increase in liver carcinoma in male mice and liver adenoma in female mice at 3 times the maximum recommended human dose.
  Electron microscopy studies have demonstrated peroxisomal proliferation following fenofibrate administration to the rat. An adequate study to test for peroxisome proliferation in humans has not been done, but changes in peroxisome morphology and numbers have been observed in humans after treatment with other members of the fibrate class when liver biopsies were compared before and after treatment in the same individual.
  Fenofibrate has been demonstrated to be devoid of mutagenic potential in the following tests: Ames, mouse lymphoma, chromosomal aberration and unscheduled DNA synthesis.
  Pregnancy Category C: Fenofibrate has been shown to be embryocidal and teratogenic in rats when given in doses 7 to 10 times the maximum recommended human dose and embryocidal in rabbits when given at 9 times the maximum recommended human dose (on the basis of mg/meter2 surface area). There are no adequate and well-controlled studies in pregnant women. Fenofibrate should be used during pregnancy only if the potential benefit justifies the potential risk to the fetus.
  Administration of 9 times the maximum recommended human dose of fenofibrate to female rats before and throughout gestation caused 100% of dams to delay delivery and resulted in a 60% increase in post-implantation loss, a decrease in litter size, a decrease in birth weight, a 40% survival of pups at birth, a 4% survival of pups as neonates, and a 0% survival of pups to weaning, and an increase in spina bifida.
  Administration of 10 times the maximum recommended human dose to female rats on days 6 to 15 of gestation caused an increase in gross, visceral and skeletal findings in fetuses (domed head/hunched shoulders/rounded body/abnormal chest, kyphosis, stunted fetuses, elongated sternal ribs, malformed sternebrae, extra foramen in palatine, misshapen vertebrae, supernumerary ribs).
  Administration of 7 times the maximum recommended human dose to female rats from day 15 of gestation through weaning caused a delay in delivery, a 40% decrease in live births, a 75% decrease in neonatal survival, and decreases in pup weight, at birth as well as on days 4 and 21 post-partum.
  Administration of 9 and 18 times the maximum recommended human dose to female rabbits caused abortions in 10% of dams at 9 times and 25% of dams at 18 times the maximum recommended human dose and death of 7% of fetuses at 18 times the maximum recommended human dose.
  Nursing Mothers
  Fenofibrate should not be used in nursing mothers. Because of the potential for tumorigenicity seen in animal studies, a decision should be made whether to discontinue nursing or to discontinue the drug.
  Pediatric Use
  Safety and efficacy in pediatric patients have not been established.
  Geriatric Use
  Fenofibric acid is known to be substantially excreted by the kidney, and the risk of adverse reactions to this drug may be greater in patients with impaired renal function. Because elderly patients are more likely to have decreased renal function, care should be taken in dose selection.

ADVERSE REACTIONS SECTION

- CLINICAL: Adverse events reported by 2% or more of patients treated with fenofibrate during the double-blind, placebo-controlled trials, regardless of causality, are listed in the table below. Adverse events led to discontinuation of treatment in 5% of patients treated with fenofibrate and in 3% treated with placebo. Increases in liver function tests were the most frequent events, causing discontinuation of fenofibrate treatment in 1.6% of patients in double-blind trials.
  BODY SYSETM | Fenofibrate* | Placebo
  Adverse Event | (N = 489) | (N = 365)
  BODY AS A WHOLE
  Abdominal Pain | 4.6% | 4.4%
  Back Pain | 3.4% | 2.5%
  Headache | 3.2% | 2.7%
  Asthenia | 2.1% | 3%
  Flu Syndrome | 2.1% | 2.7%
  DIGESTIVE
  Liver Function Tests Abnormal | 7.5%** | 1.4%
  Diarrhea | 2.3% | 4.1%
  Nausea | 2.3% | 1.9%
  Constipation | 2.1% | 1.4%
  METABOLIC AND NUTRITIONAL DISORDERS
  SGPT Increased | 3% | 1.6%
  Creatine Phosphokinase Increased | 3% | 1.4%
  SGOT Increased | 3.4%** | 0.5%
  RESPIRATORY
  Respiratory Disorder | 6.2% | 5.5%
  Rhinitis | 2.3% | 1.1%
  *Dosage equivalent to 200 mg fenofibrate tablets.
  **Significantly different from Placebo.
  Additional adverse events reported by three or more patients in placebo-controlled trials or reported in other controlled or open trials, regardless of causality are listed below.
  BODY AS A WHOLE: Chest pain, pain (unspecified), infection, malaise, allergic reaction, cyst, hernia, fever, photosensitivity reaction, and accidental injury.
  CARDIOVASCULAR SYSTEM: Angina pectoris, hypertension, vasodilatation, coronary artery disorder, electrocardiogram abnormal, ventricular extrasystoles, myocardial infarct, peripheral vascular disorder, migraine, varicose vein, cardiovascular disorder, hypotension, palpitation, vascular disorder, arrhythmia, phlebitis, tachycardia, extrasystoles, and atrial fibrillation.
  DIGESTIVE SYSTEM: Dyspepsia, flatulence, nausea, increased appetite, gastroenteritis, cholelithiasis, rectal disorder, esophagitis, gastritis, colitis, tooth disorder, vomiting, anorexia, gastrointestinal disorder, duodenal ulcer, nausea and vomiting, peptic ulcer, rectal hemorrhage, liver fatty deposit, cholecystitis, eructation, gamma glutamyl transpeptidase, and diarrhea.
  ENDOCRINE SYSTEM: Diabetes mellitus
  HEMIC AND LYMPHATIC SYSTEM: Anemia, leukopenia, ecchymosis, eosinophilia, lymphadenopathy, and thrombocytopenia.
  METABOLIC AND NUTRITIONAL DISORDERS: Creatinine increased, weight gain, hypoglycemia, gout, weight loss, edema, hyperuricemia, and peripheral edema.
  MUSCULOSKELETAL SYSTEM: Myositis, myalgia, arthralgia, arthritis, tenosynovitis, joint disorder, arthrosis, leg cramps, bursitis, and myasthenia.
  NERVOUS SYSTEM: Dizziness, insomnia, depression, vertigo, libido decreased, anxiety, paresthesia, dry mouth, hypertonia, nervousness, neuralgia, and somnolence.
  RESPIRATORY SYSTEM: Pharyngitis, bronchitis, cough increased, dyspnea, asthma, pneumonia, laryngitis, and sinusitis.
  SKIN AND APPENDAGES: Rash, pruritus, eczema, herpes zoster, urticaria, acne, sweating, fungal dermatitis, skin disorder, alopecia, contact dermatitis, herpes simplex, maculopapular rash, nail disorder, and skin ulcer.
  SPECIAL SENSES: Conjunctivitis, eye disorder, amblyopia, ear pain, otitis media, abnormal vision, cataract specified, and refraction disorder.
  UROGENITAL SYSTEM: Urinary frequency, prostatic disorder, dysuria, kidney function abnormal, urolithiasis, gynecomastia, unintended pregnancy, vaginal moniliasis, and cystitis.

OVERDOSAGE SECTION

There is no specific treatment for overdose with fenofibrate tablets. General supportive care of the patient is indicated, including monitoring of vital signs and observation of clinical status, should an overdose occur. If indicated, elimination of unabsorbed drug should be achieved by emesis or gastric lavage; usual precautions should be observed to maintain the airway. Because fenofibrate is highly bound to plasma proteins, hemodialysis should not be considered.

DOSAGE & ADMINISTRATION SECTION

Patients should be placed on an appropriate lipid-lowering diet before receiving fenofibrate tablets, and should continue this diet during treatment with fenofibrate tablets. Fenofibrate tablets should be given with meals, thereby optimizing the bioavailability of the medication.

For the treatment of adult patients with primary hypercholesterolemia or mixed hyperlipidemia, the initial dose of fenofibrate tablets is 160 mg per day.

For adult patients with hypertriglyceridemia, the initial dose is 54 to 160 mg per day. Dosage should be individualized according to patient response, and should be adjusted if necessary following repeat lipid determinations at 4 to 8 week intervals. The maximum dose is 160 mg per day.

Treatment with fenofibrate tablets should be initiated at a dose of 54 mg/day in patients having impaired renal function, and increased only after evaluation of the effects on renal function and lipid levels at this dose. In the elderly, the initial dose should likewise be limited to 54 mg/day.

Lipid levels should be monitored periodically and consideration should be given to reducing the dosage of fenofibrate tablets if lipid levels fall significantly below the targeted range.